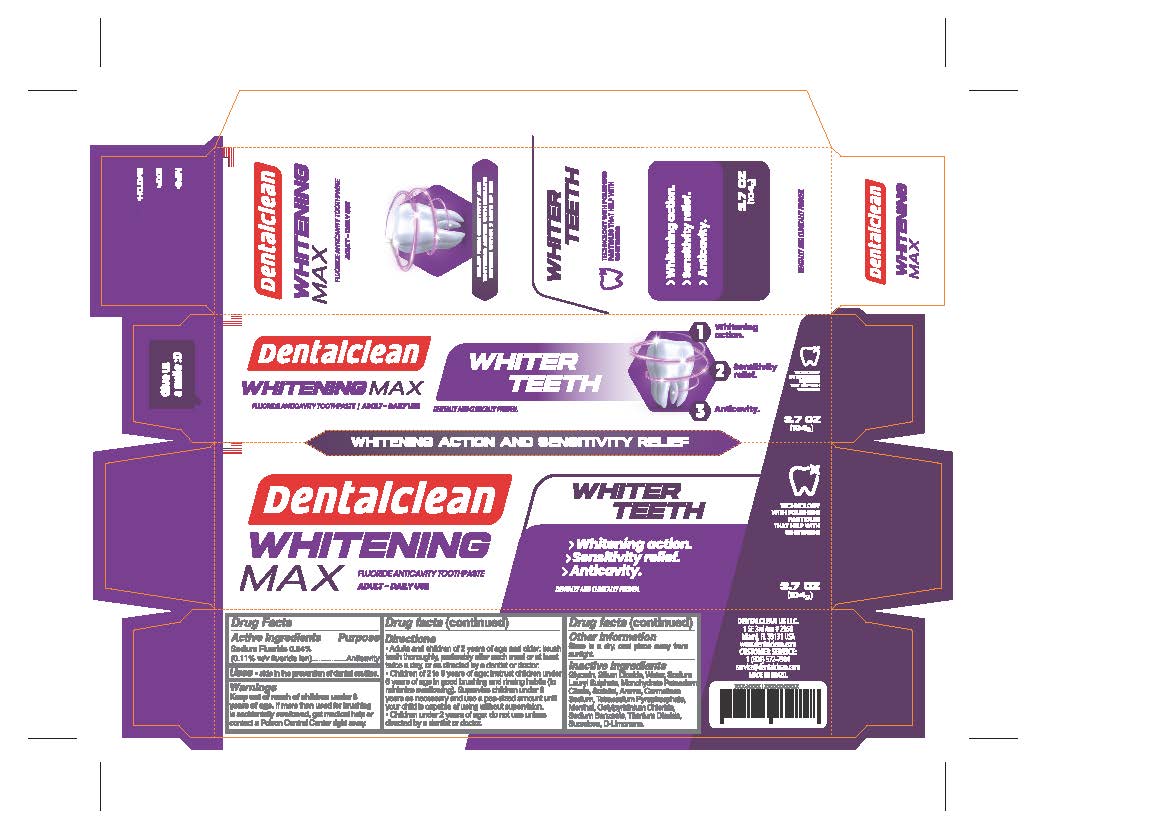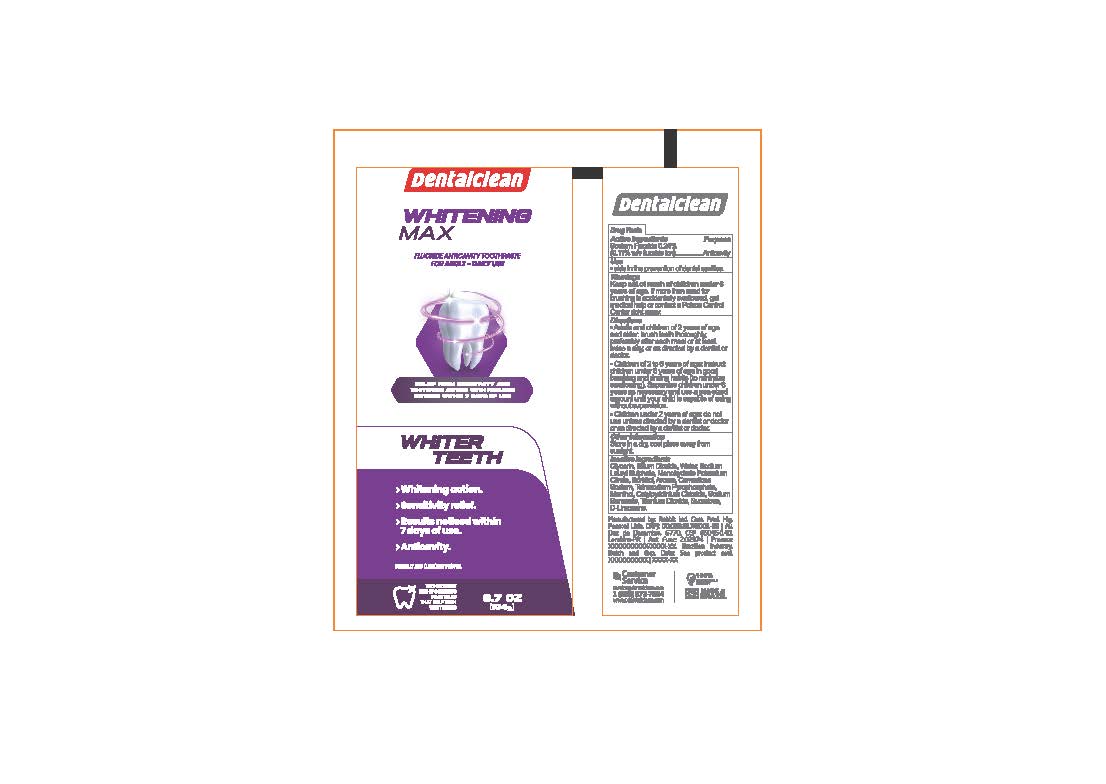 DRUG LABEL: Dentalclean Whitening Max
NDC: 84035-004 | Form: PASTE, DENTIFRICE
Manufacturer: Rabbit Indústria e Comércio de Produtos de Higiene Pessoal Ltda
Category: otc | Type: HUMAN OTC DRUG LABEL
Date: 20240507

ACTIVE INGREDIENTS: SODIUM FLUORIDE 2.4 mg/1 g
INACTIVE INGREDIENTS: MENTHOL; SUCRALOSE; CETYLPYRIDINIUM CHLORIDE ANHYDROUS; SODIUM LAURYL SULFATE; WATER; SILICON DIOXIDE; SORBITOL; POTASSIUM CITRATE; CARBOXYMETHYLCELLULOSE SODIUM, UNSPECIFIED FORM; GLYCERIN; SODIUM BENZOATE; TITANIUM DIOXIDE; SODIUM PYROPHOSPHATE; LIMONENE, (+/-)-

Dentalclean Whitening Max

ACTIVE INGREDIENT

Sodium fluoride 0.24%

PURPOSE

Anticavity

INDICATIONS AND USAGE

Useaids in the prevention of dental cavities

WARNINGS

WARNINGS: If more than used for brushing is accidentally swallowed, get medical help or contact poison control center right away.

Directions

- Adults and children 2 years of age and older: brush teeth thoroughly, preferably after each meal or at least twice a day, or as directed by a dentist or doctor.

• Children 2 to 6 years of age: instruct children under 6 years of age in good brushing and rinsing habits (to minimize swallowing). Supervise children under 6 years as necessary and use a pea-sized amount until your child is capable of using without supervision.

• Children under 2 years of age: do not use unless directed by a dentist or doctor or as directed by a dentist or doctor.

OTHER SAFETY INFORMATION

Store in a dry, cool place away from sunlight.

Inactive Ingredients

Glycerin, Silium Dioxide, Water, Sodium Lauryl Sulphate, Monohydrate Potassium Citrate, Sorbitol, Aroma, Carmetlose Sodium, Tetrasodium Pyrophosphate, Menthol, Cetytpyridinium Chloride, Sodium Benzoate, Titanium Dioxide, Sucralose, D-Limonene.

Keep out of reach of children under 6 years of age